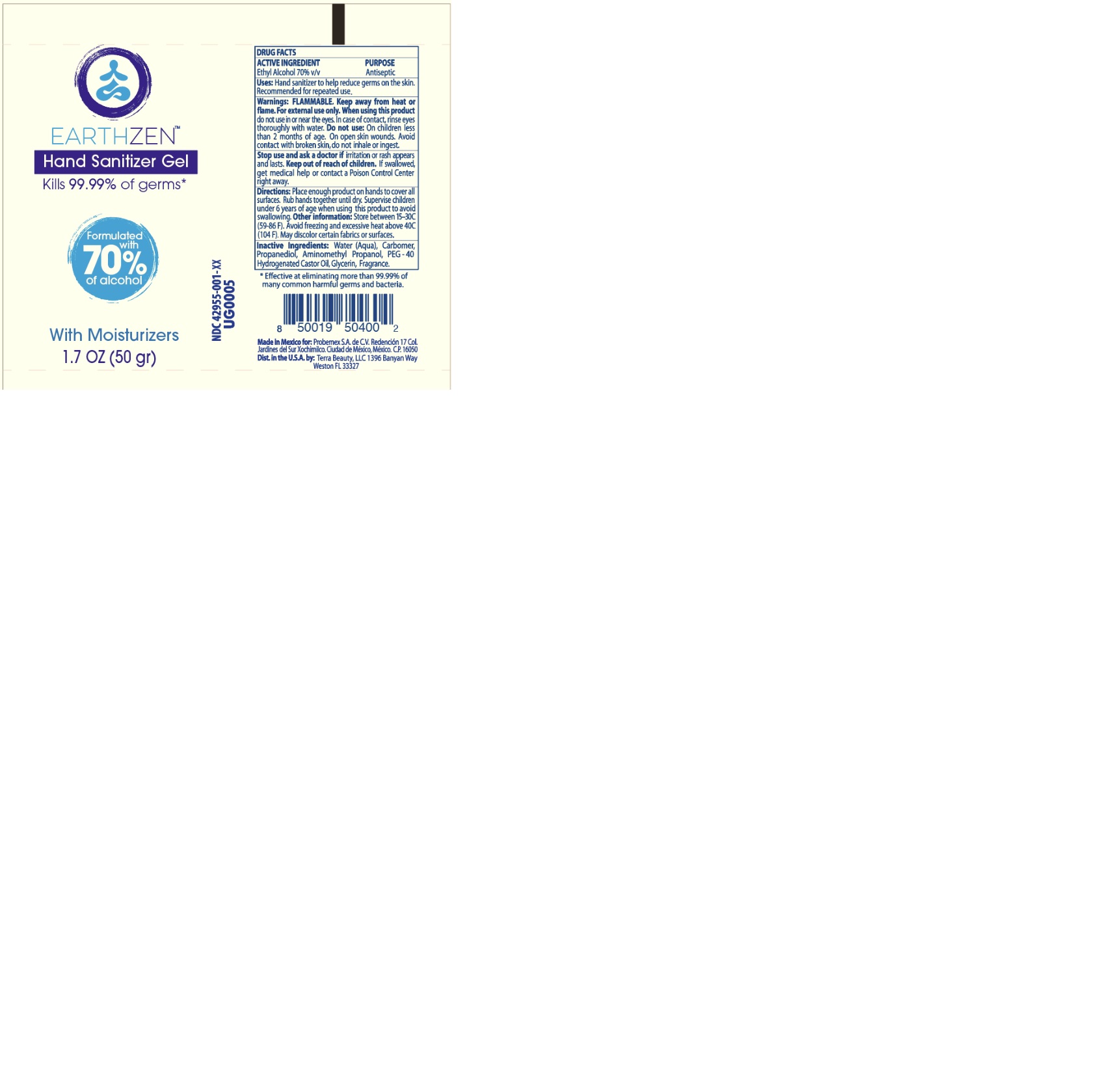 DRUG LABEL: HAND SANITIZER EARTHZEN
NDC: 42955-011 | Form: GEL
Manufacturer: PROBEMEX S.A. DE CV
Category: otc | Type: HUMAN OTC DRUG LABEL
Date: 20200812

ACTIVE INGREDIENTS: ALCOHOL 70 mL/100 mL
INACTIVE INGREDIENTS: AMINOMETHYL PROPANEDIOL 0.22 mL/100 mL; WATER 27.9 mL/100 mL; HYDROGENATED CASTOR OIL 0.14 mL/100 mL; GLYCERIN 0.001 mL/100 mL; PROPANEDIOL 0.51 mL/100 mL; CARBOXYPOLYMETHYLENE 0.33 mL/100 mL

HAND SANITIZER EARTHZEN

ACTIVE INGRIDIENT

ETHYL ALCOHOL 70%

PURPOSE

ANTISEPTIC

STOP USE

STOP USE AND ASK A DOCTOR IF IRRITATION OR RASH APPEARS AND LAST. KEEP OUT OF REACH OF CHILDREN. IF SWALLOWED GET MEDICAL HELP OR CONTACT A POISON CONTROL CENTER RIGHT AWAY

WARNING

WARNINGS: FLAMMABLE KEEP AWAY FROM HEAT OR FLAME. FOR EXTERNAL USE ONLY. WHEN USING THIS PRODUCT DO NOT USE IN OR NEAR THE YES. IN CASE OF CONTACT RINSE EYE THRROUGHLY WITH WATER

DO NOT USE ON CHILDREN LESS THAN 2 MONTHS OF AGE. OPEN SKIN WOUNDS AVOID CONTACT WIITH BROKER SKIN

DIRECTIONS

PLACE ENOUGH PRODUCTO NO HANDS TO COVER ALL SUFACES. RUB HANDS TOGETHER UNTIL DRY.

SUPERVISE CHILDREN UNDER 6 YEARS OF AGE WHEN USING THIS PRODUCT TO AVOID SWALLOWING

OTHER INFORMATION: STORE BETWEEN 15-30C. AVOID FREEZING AND EXCESSIVE HEAT ABOCE 40C

MAY DISCOLOR CERTAIN FABRIC OR SUFACES

INACTIVE

WATER, CARBOMER PROPANEDIOL AMINOMETHYL PROPANOL PEG 40 HYDROGENATED CASTOR OIL GLYCERIN

WARNING

WARNING FLAMMABLE KEEP AWAY FROM HEAT

DOSAGE

PLACE ENOUGH PRODUCT ON HANDS TO COVER ALL SURFACE

KEEP OUT OF REACH OF CHILDREN

PACKAGE

42955-011-01

42955-011-02

42955-011-03